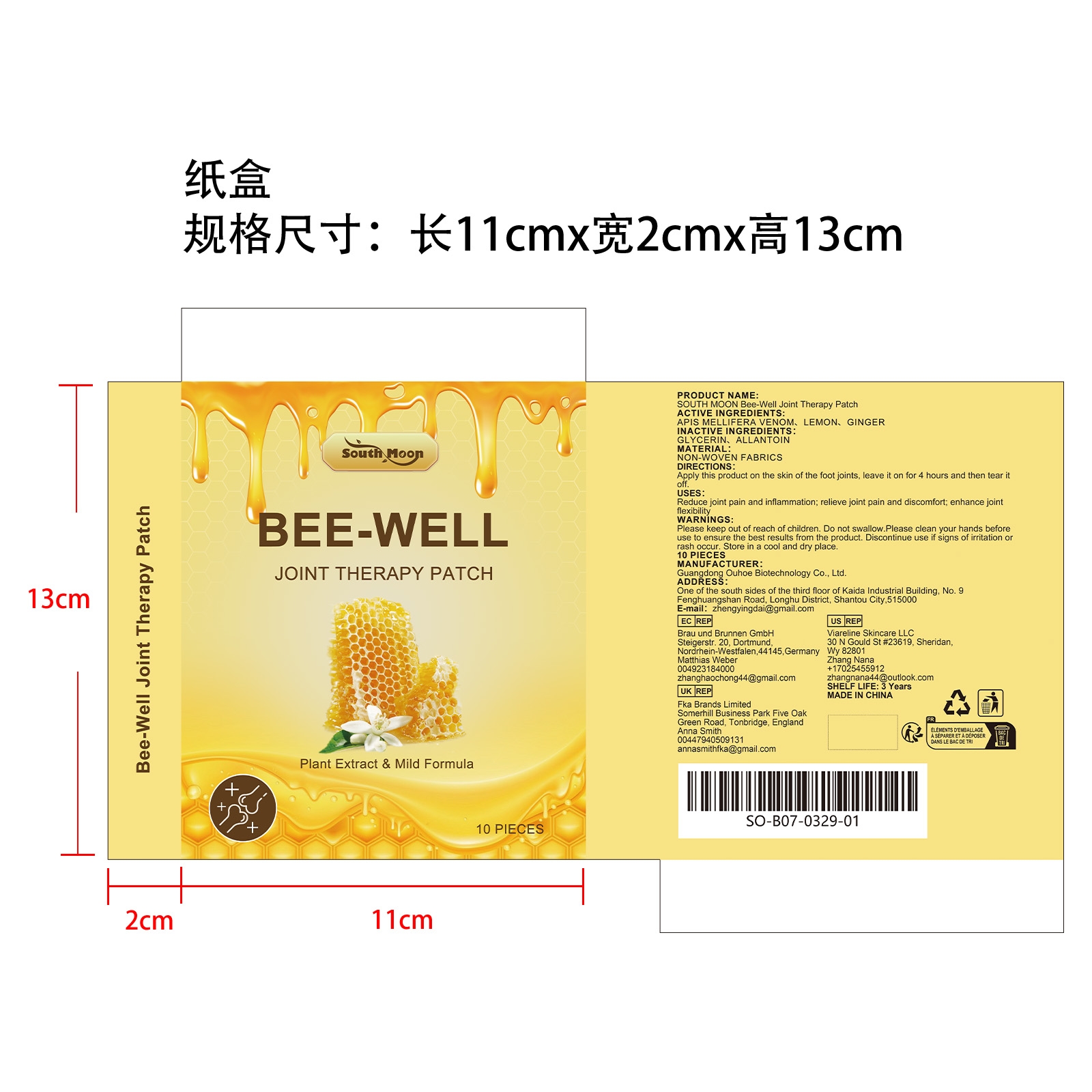 DRUG LABEL: SOUTH MOON Bee-Well Joint Therapy Patch
NDC: 84744-059 | Form: PATCH
Manufacturer: Guangdong Ouhoe Biotechnology Co., Ltd.
Category: otc | Type: HUMAN OTC DRUG LABEL
Date: 20241023

ACTIVE INGREDIENTS: APIS MELLIFERA VENOM 3 g/10 g; LEMON 1 g/10 g; GINGER 1.5 g/10 g
INACTIVE INGREDIENTS: GLYCERIN 1.5 g/10 g; ALLANTOIN 3 g/10 g

ACTIVE INGREDIENTS

APIS MELLIFERA VENOM,
LEMON,
GINGER

PURPOSE

Reduce joint pain and inflammation; relieve joint pain and discomfort; enhance joint flexibility

USE

Apply this product on the skin of the foot joints, leave it on for 4 hours and then tear it off.

WARNINGS

Please keep out of reach of children. Do not swallow. Please clean your hands before use to ensure the best results from the product. Discontinue use if signs of irritation or rash occur. Store in a cool and dry place.

STOP USE

Discontinue use if signs of irritation or rash occur.

DO NOT USE

Discontinue use if signs of irritation or rash occur.

KEEP OUT OF REACH OF CHILDREN

Please keep out of reach of children. Do not swallow.

STORAGE AND HANDLING

Store in a cool and dry place.

INACTIVE INGREDIENT

GLYCERIN、ALLANTOIN